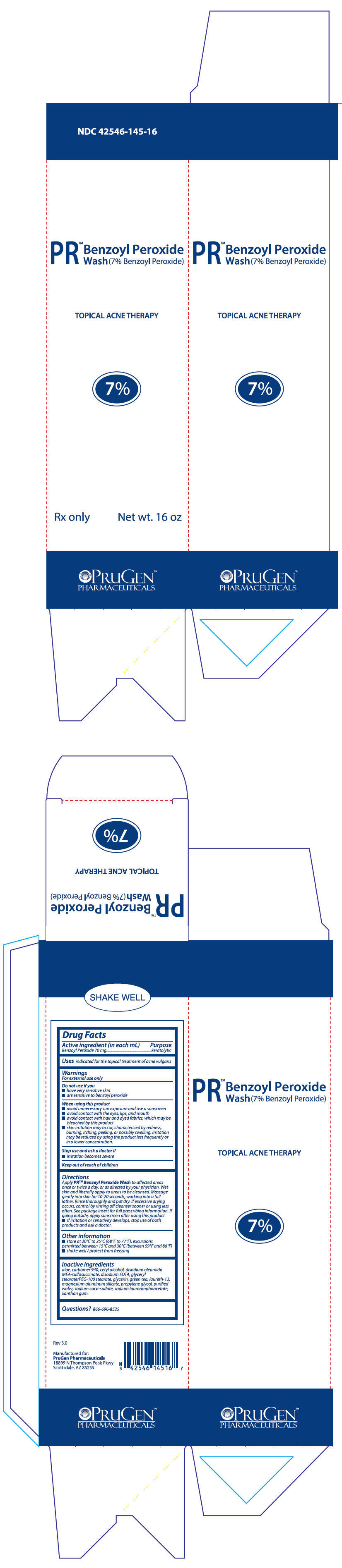 DRUG LABEL: PR Benzoyl Peroxide Wash
NDC: 42546-145 | Form: LOTION
Manufacturer: PruGen, Inc.
Category: prescription | Type: HUMAN PRESCRIPTION DRUG LABEL
Date: 20180612

ACTIVE INGREDIENTS: Benzoyl Peroxide 70 mg/1 mL
INACTIVE INGREDIENTS: aloe; CARBOMER HOMOPOLYMER TYPE C (ALLYL PENTAERYTHRITOL CROSSLINKED); cetyl alcohol; DISODIUM OLEAMIDO MONOETHANOLAMINE SULFOSUCCINATE; EDETATE DISODIUM ANHYDROUS; PEG-100 STEARATE; GLYCERYL MONOSTEARATE; GLYCERIN; GREEN TEA LEAF; laureth-12; magnesium aluminum silicate; propylene glycol; WATER; sodium coco-sulfate; sodium lauroamphoacetate; xanthan gum

PRTM Benzoyl Peroxide Wash Rev.1.4

DESCRIPTION:
PRTM Benzoyl Peroxide Wash is intended for topical administration and contains Benzoyl Peroxide for use in the treatment of acne vulgaris. Benzoyl Peroxide is an oxidizing agent that possesses antibacterial properties and is classified s a keratolytic. Benzoyl Peroxide (C14H10O4) is represented by the
following chemical structure:
O = C – O – O – C = O

Each mL of PRTM Benzoyl Peroxide Wash contains 70 mg of Benzoyl Peroxide in an emulsion based formulation consisting of: aloe, carbomer 940, cetyl alcohol, disodium oleamido MEA-sulfosuccinate, disodium EDTA, glyceryl stearate/PEG-100 stearate, glycerin, green tea, laureth-12, magnesium aluminum silicate, propylene glycol, purified water, sodium coco-sulfate, sodium lauroamphoacetate, xanthan gum.

CLINICAL PHARMACOLOGY:
The mechanism of action of Benzoyl Peroxide is not totally understood but its antibacterial activity against Propionibacterium acnes is thought to be a major mode of action. In addition, patients treated with Benzoyl Peroxide show a reduction in lipids and free fatty acids, and mild desquamation (drying and peeling activity) with simultaneous reduction in comedones and acne lesions. Little is known about the percutaneous penetration, metabolism, and excretion of Benzoyl Peroxide, although it has been shown that Benzoyl Peroxide absorbed by the skin is metabolized to benzoic acid and then excreted as benzoate in the urine. There is no evidence of systemic toxicity caused by Benzoyl Peroxide in humans.

INDICATIONS AND USAGE:
PRTM Benzoyl Peroxide Wash is indicated for the topical treatment of acne vulgaris.

CONTRAINDICATIONS:
PRTM Benzoyl Peroxide Wash is contraindicated in persons with a known hypersensitivity to any of its ingredients.

WARNINGS:
When using this product, avoid unnecessary sun exposure and use a sunscreen.
PRECAUTIONS:
General: For external use only. If severe irritation develops, discontinue use and institute appropriate therapy. After reaction clears, treatment may often be resumed with less frequent application. These preparations should not be used in or near the eyes or on mucous membranes.

Information For Patients:
Avoid contact with eyes, eyelids, lips and mucous membranes. If accidental contact occurs, rinse with water. Contact with any colored material (including hair and fabric) may result in bleaching or discoloration. If excessive irritation develops, discontinue use and consult your physician.

Carcinogensesis, Mutagenesis, Impairment of Fertility:
Data from several studies employing a strain of mice that is highly susceptible to developing cancer suggest that Benzoyl Peroxide acts as a tumor promoter. The clinical significance of these findings to humans is unknown. Benzoyl Peroxide has not been found to be mutagenic (Ames Test) and there are no published data indicating it impairs fertility.

Pregnancy: Teratogenic Effects:
Pregnancy Category C: Animal reproduction studies have not been conducted with Benzoyl Peroxide. It is not known whether Benzoyl Peroxide can cause fetal harm when administered to a pregnant woman or can affect reproduction capacity. Benzoyl Peroxide should be used by a pregnant woman only if clearly needed. There are no available data on the effect of Benzoyl Peroxide on the later growth, development and functional maturation of the unborn child.

ADVERSE REACTIONS:
Allergic contact dermatitis and dryness have been reported with topical Benzoyl Peroxide therapy.

OVERDOSAGE:
If excessive scaling, erythema or edema occurs, the use of this preparation should be discontinued. To hasten resolution of the adverse effects, cool compresses may be used. After symptoms and signs subside, a reduced dosage schedule may be cautiously tried if the reaction is judged to be due to excessive use and not allergenicity.

DOSAGE AND ADMINISTRATION:
PRTM Benzoyl Peroxide Wash: Apply to affected areas once or twice a day, or as directed by your physician. Wet skin and liberally apply to areas to be cleansed. Massage gently into skin for 10-20 seconds, working into a full lather. Rinse thoroughly and pat dry. If excessive drying occurs, control by rinsing of cleanser sooner or using less often.

HOW SUPPLIED:
PRTM Benzoyl Peroxide Wash is supplied in a 16 oz bottle, NDC 42546-145-16.

STORAGE AND HANDLING

Store at controlled room temperature 20°-25° C (68°-77° F); excursions permitted to 15°-30°C (59°-86°F).
Protect from freezing.

KEEP THIS AND ALL MEDICATIONS OUT OF THE REACH OF CHILDREN.

PRINCIPAL DISPLAY PANEL - 473 mL Bottle Box

NDC 42546-145-16

PR™
Benzoyl Peroxide
Wash (7% Benzoyl Peroxide)

TOPICAL ACNE THERAPY

7%

Rx only
Net wt. 16 oz

PRUGEN™
PHARMACEUTICALS